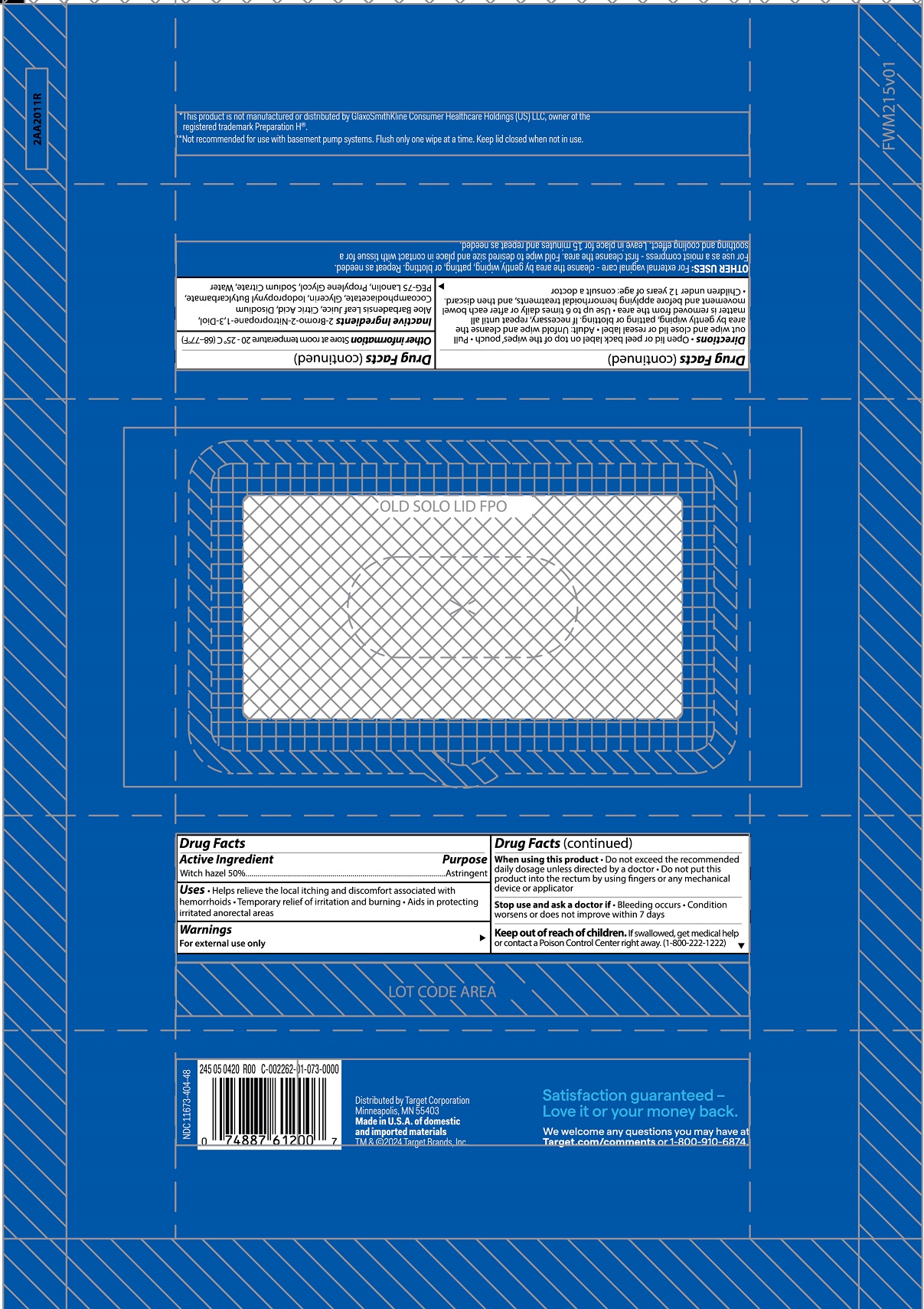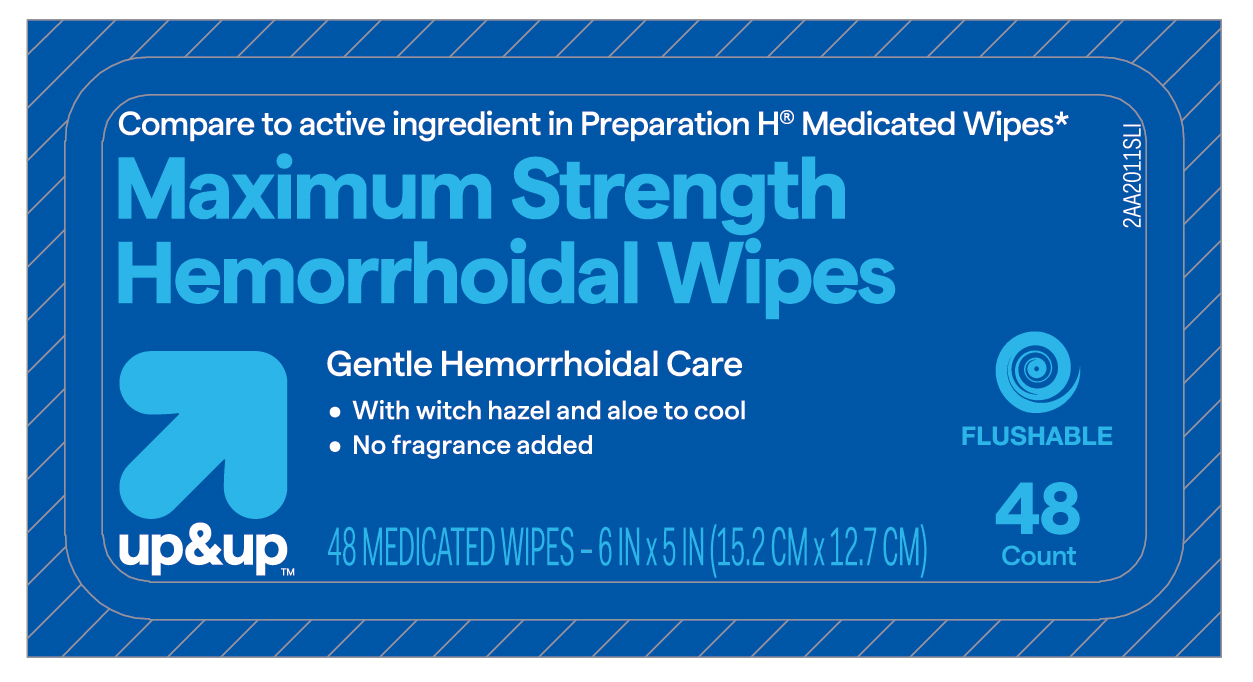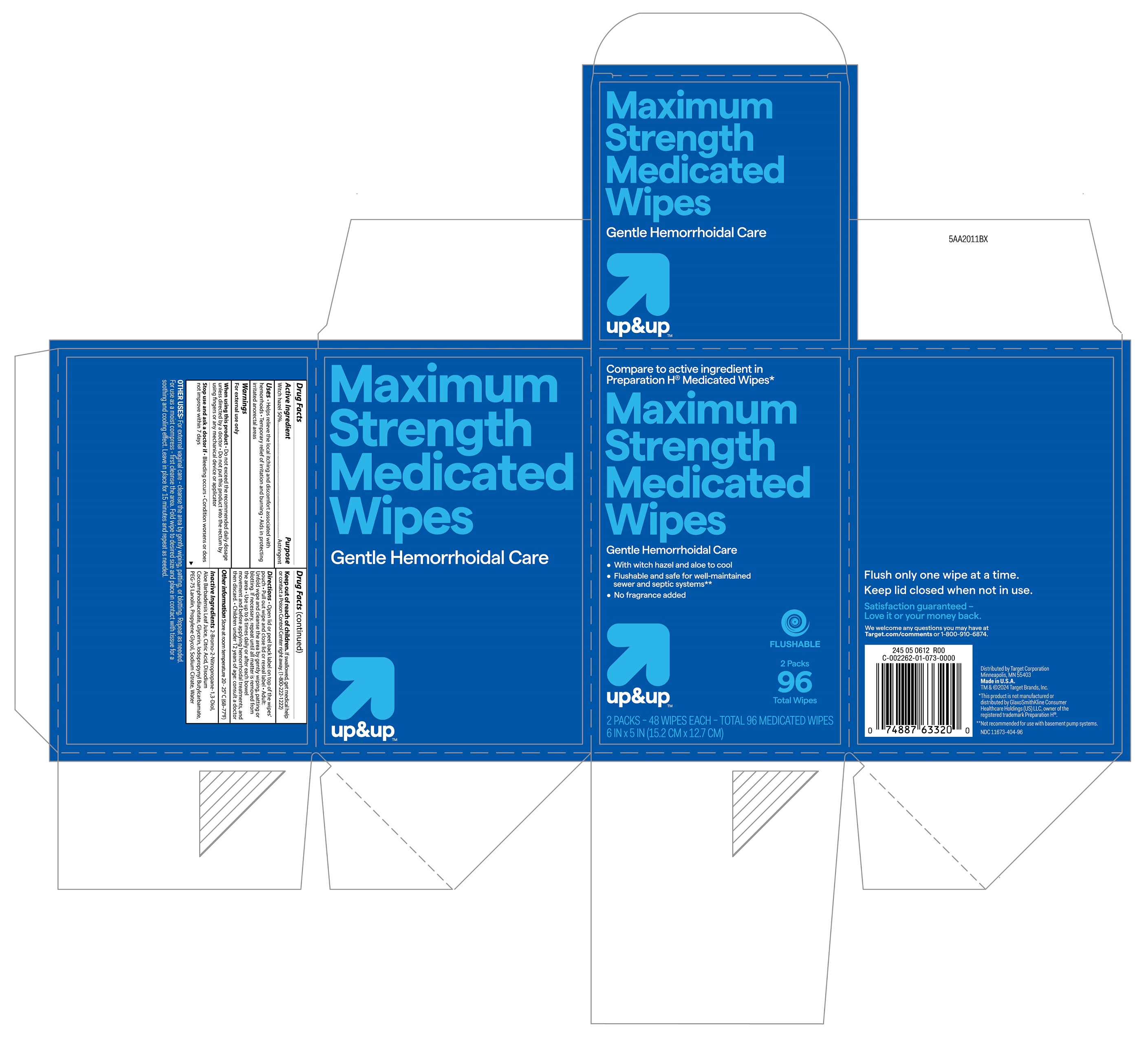 DRUG LABEL: up and up medicated wipes
NDC: 11673-404 | Form: SWAB
Manufacturer: Target Corporation
Category: otc | Type: HUMAN OTC DRUG LABEL
Date: 20241107

ACTIVE INGREDIENTS: WITCH HAZEL 0.5 g/1 g
INACTIVE INGREDIENTS: ANHYDROUS CITRIC ACID; PROPYLENE GLYCOL; SODIUM CITRATE; BRONOPOL; GLYCERIN; ALOE VERA LEAF; DISODIUM COCOAMPHODIACETATE; IODOPROPYNYL BUTYLCARBAMATE; PEG-75 LANOLIN; WATER

Target up and up Medicated Wipes NDC 11673-404

Active ingredient

Witch hazel 50%

Purpose

Astringent

Uses

- helps relieve the local itching and discomfort associated with hemorrhoids
- temporary relief of irritation and burning
- aids in protecting irritated anorectal areas

Warnings

For external use only

When using this product

- do not exceed the recommended daily dosage unless directed by a doctor
- do not put this product into the rectum by using fingers or any mechanical device or applicator

Stop use and ask a doctor if

- bleeding occurs
- condition worsens or does not improve within 7 days

Keep out of reach of children.

If swallowed, get medical help or contact a Poison Control Center right away.(1-800-222-1222)

Directions

- adult: unfold wipe and cleanse the area by gently wiping, patting or blotting. If necessary, repeat until all matter is removed from the area.
- Use up to 6 times daily or after each bowel movement and before applying topical hemorrhoidal treatments, and then discard
- children under 12 years of age: consult a doctor

Other information

store at room temperature 20-25ºC (68-77ºF)

Inactive ingredients

2-Bromo-2-Nitropropane-1,3-Diol, Aloe Barbadensis Leaf Juice, Citric Acid, Disodium Cocoamphodiacetate, Glycerin, Iodopropynyl Butylcarbamate, PEG-75 Lanolin, Propylene Glycol, Sodium Citrate, Water

Principal display panel- 48 count

Compare to active ingredient in Preparation H Medicated Wipes

Maximum strength medicated wipes

gentle hemorrhoidal care

with witch hazel and aloe to cool, soother and comfort

48 medicated wipes

6 in x 5in (15.2cm x 12.7 cm)

Other Uses:
• for vaginal care - cleanse the area by gently wiping, patting or blotting. Repeat as needed.
• for use as a moist compress - if necessary, first cleanse the area as previously described. Fold wipe to desired size and place in contact with tissue for a soothing and cooling effect. Leave in place for 15 minutes and repeat as needed.

Flowrap of 48 counts:

lid

Box of 96 counts containing 2 flowraps: